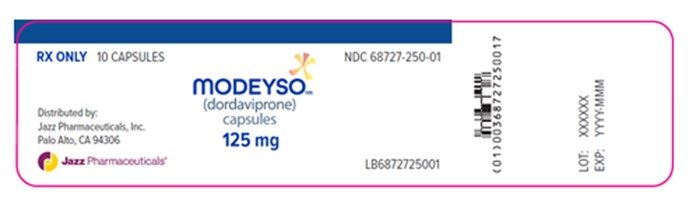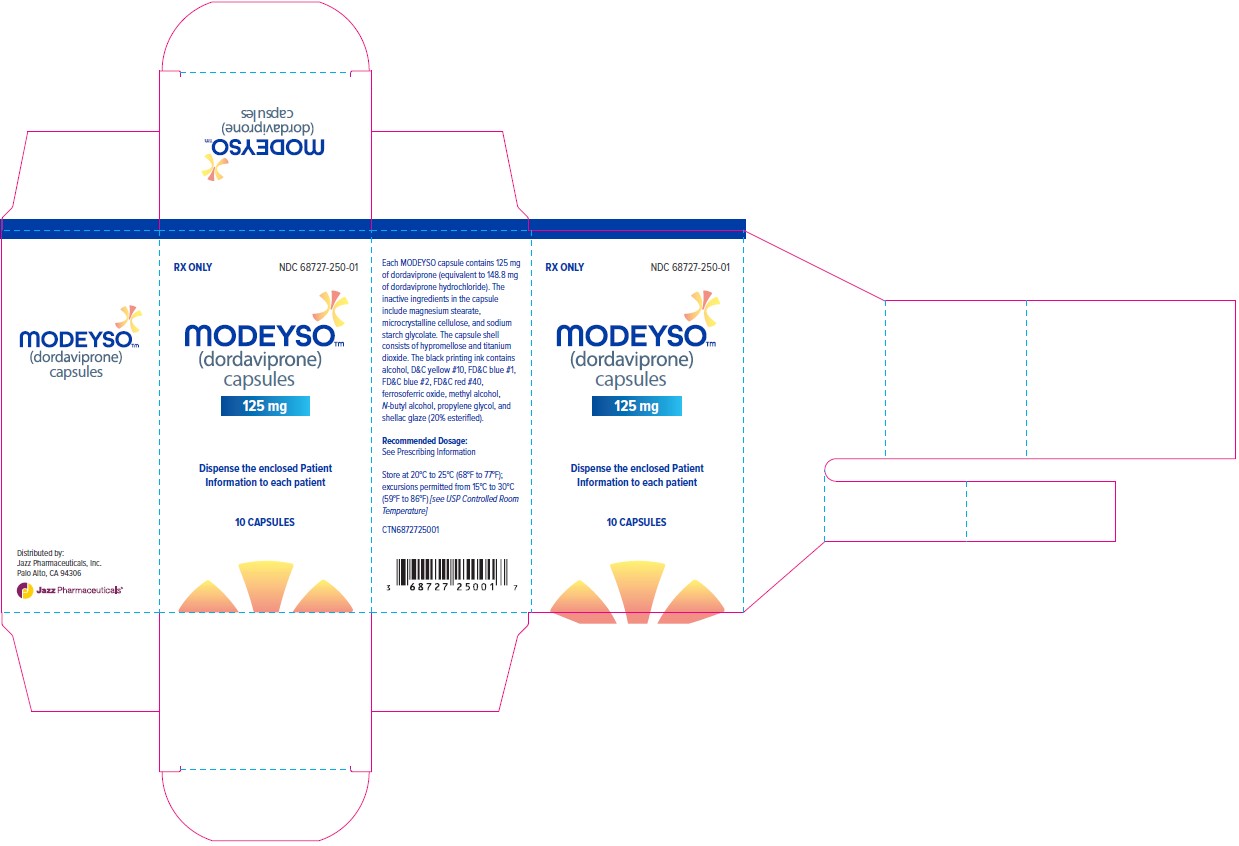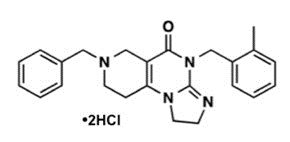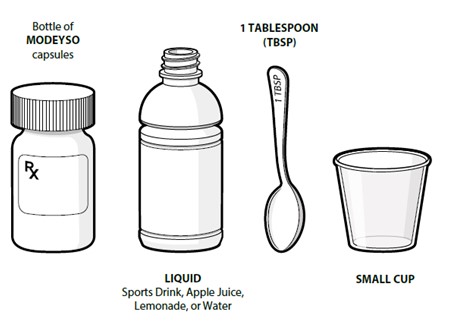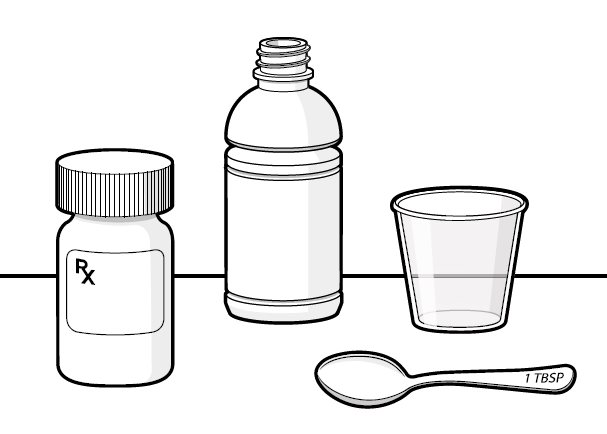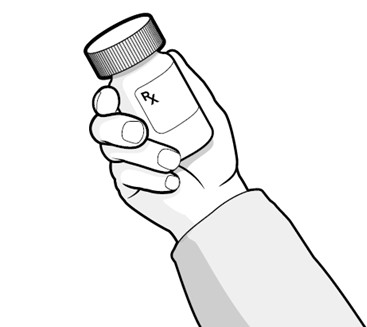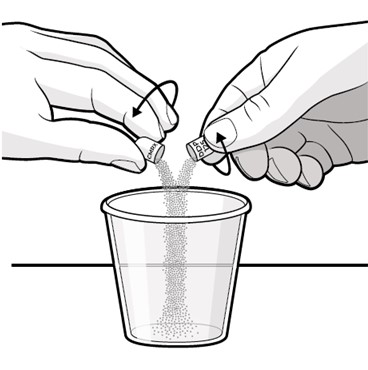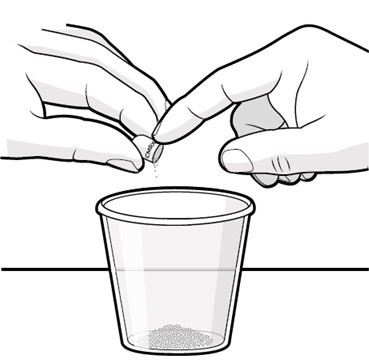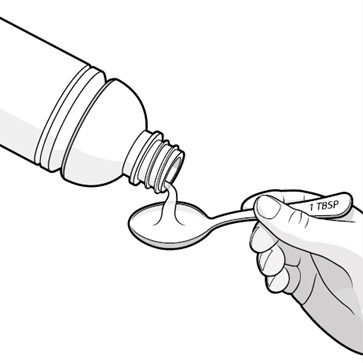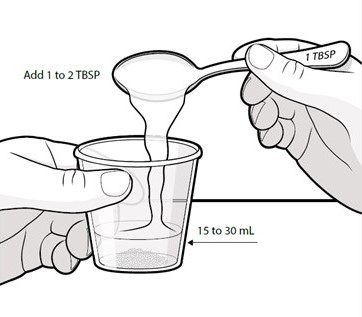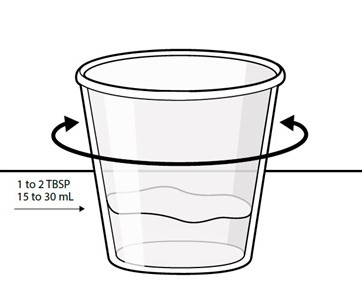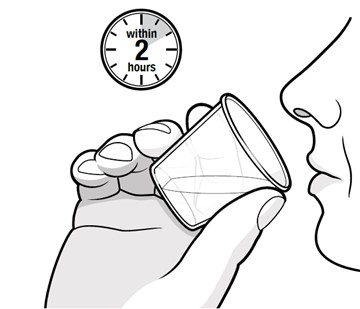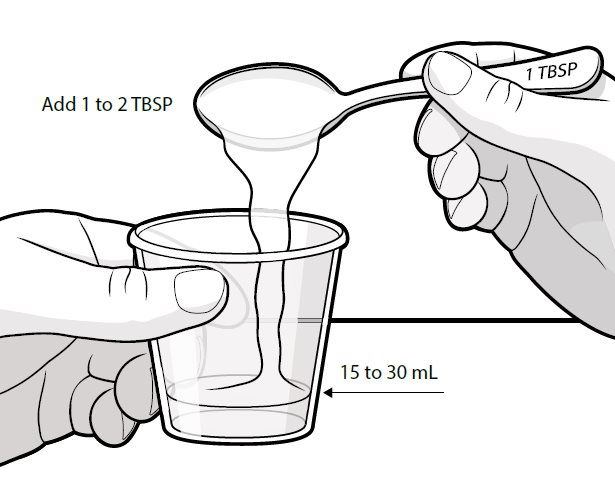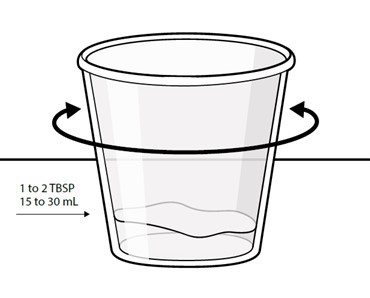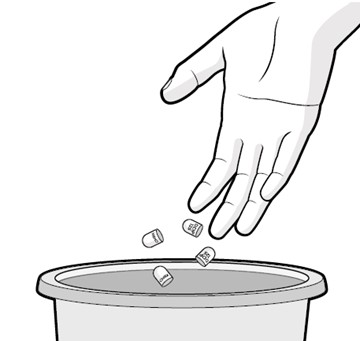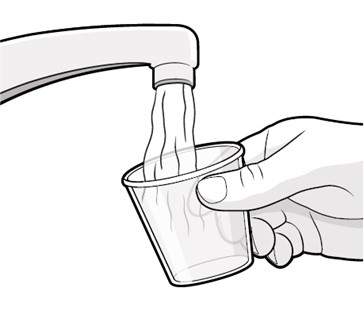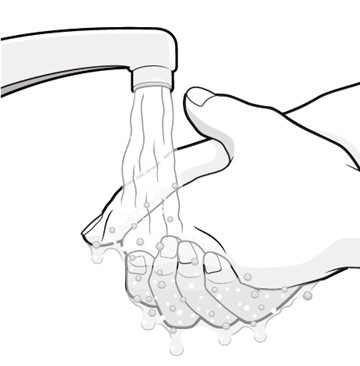 DRUG LABEL: MODEYSO
NDC: 68727-250 | Form: CAPSULE
Manufacturer: Jazz Pharmaceuticals, Inc.
Category: prescription | Type: HUMAN PRESCRIPTION DRUG LABEL
Date: 20250808

ACTIVE INGREDIENTS: DORDAVIPRONE 125 mg/1 1
INACTIVE INGREDIENTS: MICROCRYSTALLINE CELLULOSE 112; SODIUM STARCH GLYCOLATE TYPE A POTATO; MAGNESIUM STEARATE

HIGHLIGHTS OF PRESCRIBING INFORMATION

These highlights do not include all the information needed to use MODEYSO safely and effectively. See full prescribing information for MODEYSO.
MODEYSO™ (dordaviprone) capsules, for oral use
Initial U.S. Approval: 2025

1 INDICATIONS AND USAGE

MODEYSO is a protease activator indicated for the treatment of adult and pediatric patients 1 year of age and older with diffuse midline glioma harboring an H3 K27M mutation with progressive disease following prior therapy. (1)

This indication is approved under accelerated approval based on response rate and duration of response [see Clinical Studies (14)]. Continued approval for this indication may be contingent upon verification and description of clinical benefit in a confirmatory trial(s).

2 DOSAGE AND ADMINISTRATION

- Select patients for treatment with MODEYSO based on the presence of an H3 K27M mutation from tumor specimens. (2.1)
- Monitor ECG and electrolytes before starting MODEYSO and periodically during treatment as clinically indicated. (2.2)
- The recommended dose in adult patients is 625 mg orally once weekly. (2.3)
- The recommended dose in pediatric patients weighing ≥10 kg is based on body weight (see Table 1). (2.3)
- Take MODEYSO orally once weekly on an empty stomach (at least 1 hour before or 3 hours after food intake). (2.3)
- Continue MODEYSO until disease progression or unacceptable toxicity. (2.3)

3 DOSAGE FORMS AND STRENGTHS

- Capsules: 125 mg (3)

4 CONTRAINDICATIONS

None. (4)

5 WARNINGS AND PRECAUTIONS

- Hypersensitivity: If clinically significant hypersensitivity or anaphylaxis occur, immediately discontinue MODEYSO and initiate appropriate medical treatment and supportive care. (5.1)
- QTc Interval Prolongation: MODEYSO causes concentration dependent QTc interval prolongation. Interrupt or reduce the dose of MODEYSO in patients who develop QT prolongation, and permanently discontinue MODEYSO in patients with signs of life-threatening arrhythmias. (5.2, 12.2)
- Embryo-fetal Toxicity: Can cause fetal harm. Advise patients of the potential risk to a fetus and to use effective contraception. (5.3, 8.1, 8.3)

6 ADVERSE REACTIONS

The most common (≥20%) adverse reactions are fatigue, headache, vomiting, nausea, and musculoskeletal pain. The most common (≥2%) Grade 3 or 4 laboratory abnormalities are decreased lymphocytes, decreased calcium, and increased alanine aminotransferase. (6.1)

To report SUSPECTED ADVERSE REACTIONS, contact Chimerix at toll-free phone # 1-866-662-2679 or FDA at 1-800-FDA-1088 or www.fda.gov/medwatch.

7 DRUG INTERACTIONS

- CYP3A4 Inhibitors: Avoid concomitant use of strong and moderate CYP3A4 inhibitors with MODEYSO. If concomitant use cannot be avoided for adults and pediatric patients who weigh at least 52.5 kg, reduce the dose of MODEYSO as recommended. (2.5, 7.1)
- CYP3A4 Inducers: Avoid concomitant use of strong and moderate CYP3A4 inducers with MODEYSO. (7.1)
- Drugs Known to Prolong QTc Interval: Avoid concomitant use of MODEYSO with products known to prolong the QTc interval. If concomitant use cannot be avoided, separate administration of MODEYSO and the QT-prolonging product. (5.2, 7.2, 12.2)

8 USE IN SPECIFIC POPULATIONS

- Lactation: Advise not to breastfeed. (8.2)

FULL PRESCRIBING INFORMATION

1 INDICATIONS AND USAGE

MODEYSO is indicated for the treatment of adult and pediatric patients 1 year of age and older with diffuse midline glioma harboring an H3 K27M mutation with progressive disease following prior therapy.

This indication is approved under accelerated approval based on overall response rate and duration of response [see Clinical Studies (14)]. Continued approval for this indication may be contingent upon verification and description of clinical benefit in a confirmatory trial(s).

2 DOSAGE AND ADMINISTRATION

2.1 Patient Selection

Select patients for treatment with MODEYSO based on the presence of an H3 K27M mutation from tumor specimens [see Clinical Studies (14)]. An FDA-approved test for the detection of this mutation is not currently available.

2.2 Recommended Testing Before Starting MODEYSO

Monitor electrocardiograms (ECG) and electrolytes before starting MODEYSO and periodically during treatment as clinically indicated [see Warnings and Precautions (5.2) and Drug Interactions (7.2)].

2.3 Recommended Dosage and Administration

Take MODEYSO on an empty stomach (at least 1 hour before or 3 hours after food intake) [see Clinical Pharmacology (12.3)].

Adults

The recommended dosage of MODEYSO is 625 mg orally once weekly.

Pediatrics

The recommended dosage of MODEYSO in pediatric patients aged 1 to <17 years who weigh at least 10 kg is based on body weight (Table 1). A recommended dosage of MODEYSO has not been established in pediatric patients who weigh less than 10 kg.

Table 1: Recommended Body Weight-Based Dosage for Pediatric Patients
Body Weight (kg) | Recommended Dosage
10 kg to <12.5 kg | 125 mg Once Weekly
12.5 kg to <27.5 kg | 250 mg Once Weekly
27.5 kg to <42.5 kg | 375 mg Once Weekly
42.5 kg to <52.5 kg | 500 mg Once Weekly
≥52.5 kg | 625 mg Once Weekly

Continue MODEYSO until disease progression or unacceptable toxicity.

Swallow capsules whole. For patients unable to swallow capsules whole, open each capsule, mix contents with approximately 15 to 30 mL of liquid (sports drink, apple juice, lemonade, or water) before administration, and administer orally as a liquid [see Patient Counseling Information (17)]. Once mixed, administer within 2 hours of preparation, or discard and mix a new dose.

Vomiting

If vomiting occurs after taking a dose, do not take an additional dose and take the next dose at the regularly scheduled time.

Missed Dose

If a dose is missed within 2 days, take the missed dose as soon as possible. If a dose is missed by more than 2 days, skip the missed dose and take the next dose at the scheduled time.

2.4 Dosage Modifications for Adverse Reactions

The recommended dosage reductions for adverse reactions for MODEYSO are provided in Table 2.

Table 2: Recommended Dosage Reductions for Adverse Reactions
Patient’s Weight (kg) | First Dosage Reduction | Second Dosage Reduction
Pediatric patients 10 kg to <12.5 kg | Permanently discontinue | N/A
Pediatric patients 12.5 kg to <27.5 kg | 125 mg once weekly | Permanently discontinue
Pediatric patients 27.5 kg to <42.5 kg | 250 mg once weekly | 125 mg once weekly
Pediatric patients 42.5 kg to <52.5 kg | 375 mg once weekly | 250 mg once weekly
Pediatric patients ≥52.5 kg and adult patients | 500 mg once weekly | 375 mg once weekly

The recommended dosage modifications for adverse reactions are provided in Table 3.

Table 3: Recommended Dosage Modifications for Adverse Reactions
Adverse Reaction | Severitya | Dosage Modificationb
Hypersensitivity [see Warnings and Precautions (5.1)] | Any grade | If hypersensitivity is suspected based on clinical judgement, interrupt MODEYSO until resolution of the event.; Permanently discontinue MODEYSO in patients who develop serious hypersensitivity reactions.
QTc Interval Prolongation [see Warnings and Precautions (5.2)] | QTc absolute value >500 ms; or; An increase of >60 ms from baseline | Interrupt MODEYSO until QTc interval ≤480 ms or return to baseline.; Resume MODEYSO at the next lower dose level.
QTc Interval Prolongation [see Warnings and Precautions (5.2)] | Torsades de pointes, polymorphic ventricular tachycardia or signs or symptoms of serious or life-threatening arrhythmia | Permanently discontinue MODEYSO.
Other Adverse Reactions [see Adverse Reactions (6.1)] | Grade 3 or 4 | Interrupt MODEYSO until ≤Grade 1 or return to baseline.; Resume MODEYSO at the next lower dose level.
Other Adverse Reactions [see Adverse Reactions (6.1)] | Recurrent Grade 4 | Permanently discontinue MODEYSO.

a. National Cancer Institute Common Terminology Criteria for Adverse Events (CTCAE) Version 5.0.

b. See Table 2 for recommended dosage reductions.

2.5 Dosage Modifications for CYP3A4 Inhibitors

Avoid concomitant use of strong and moderate CYP3A4 inhibitors with MODEYSO.

- If concomitant use of a strong CYP3A4 inhibitor cannot be avoided for adult and pediatric patients who weigh at least 52.5 kg, reduce the dose of MODEYSO from 625 mg to 375 mg once weekly.
- If concomitant use of a moderate CYP3A4 inhibitor cannot be avoided for adult and pediatric patients who weigh at least 52.5 kg, reduce the dose of MODEYSO from 625 mg to 500 mg once weekly.
- The recommended dosage for pediatric patients weighing less than 52.5 kg who are receiving strong or moderate CYP3A4 inhibitors has not been established.

Upon discontinuation of the CYP3A4 inhibitor, wait for 3 to 5 plasma half-lives of the CYP3A4 inhibitor, then increase MODEYSO to the dose that was taken before starting the CYP3A4 inhibitor [see Drug Interactions (7.1) and Clinical Pharmacology (12.3)].

3 DOSAGE FORMS AND STRENGTHS

Capsules: 125 mg, white, opaque, hard capsules printed with “DDP” and “125” on the body and “CMRX” on the cap of the capsule. Each capsule contains 125 mg dordaviprone.

4 CONTRAINDICATIONS

None.

5 WARNINGS AND PRECAUTIONS

5.1 Hypersensitivity

MODEYSO can cause severe hypersensitivity reactions.

In the pooled safety population [see Adverse Reactions (6.1)], Grade 3 hypersensitivity reactions occurred in 0.3% of patients receiving MODEYSO. Signs and symptoms of hypersensitivity may include rash, hives, fever, low blood pressure, wheezing, or swelling of the face or throat.

Inform patients about the signs and symptoms of hypersensitivity reactions and instruct them to seek immediate medical attention if symptoms occur.

If clinically significant hypersensitivity or anaphylaxis occur, immediately interrupt MODEYSO and initiate appropriate medical treatment and supportive care. Based on the severity of the adverse reaction, temporarily interrupt or permanently discontinue MODEYSO [see Dosage and Administration (2.4)].

5.2 QTc Interval Prolongation

MODEYSO causes a concentration-dependent QTc interval prolongation [see Clinical Pharmacology (12.2)], which can increase the risk for ventricular tachyarrhythmias (e.g., torsades de pointes) or sudden death.

In the pooled safety population [see Adverse Reactions (6.1)], of the 82 patients who underwent at least one post-baseline ECG assessment, 6% experienced an increase in QTc of >60 msec compared to baseline after receiving MODEYSO and 1.2% had an increase in QTc to >500 msec.

Monitor ECGs and electrolytes prior to starting MODEYSO and then periodically during treatment as clinically indicated.

Significant prolongation of the QT interval may occur when MODEYSO is taken concomitantly with other products that have a known potential to prolong the QT interval. Avoid concomitant use of MODEYSO with products known to prolong the QT interval. If concomitant use cannot be avoided, separate administration of MODEYSO and the QT-prolonging product [see Drug Interactions (7.2) and Clinical Pharmacology (12.2)].

Increase the frequency of monitoring when administering MODEYSO to patients taking other products that have a known potential to prolong the QT interval and in patients with congenital long QT syndrome, existing QTc prolongation, a history of ventricular arrhythmias, electrolyte abnormalities, heart failure, or who are taking strong or moderate CYP3A4 inhibitors. Interrupt or reduce the dose of MODEYSO in patients who develop QT prolongation, and permanently discontinue MODEYSO in patients with signs of life-threatening arrhythmias [see Dosage and Administration (2.4)].

5.3 Embryo-fetal Toxicity

Based on findings from animal studies and its mechanism of action, MODEYSO can cause fetal harm when administered to a pregnant woman. In embryo-fetal development studies, oral administration of dordaviprone to pregnant rats and rabbits during organogenesis caused embryo-fetal mortality, alterations to growth, and structural abnormalities at exposures below the human exposure at the highest recommended dose.

Advise pregnant women and females of reproductive potential of the potential risk to a fetus. Advise females of reproductive potential to use effective contraception during treatment with MODEYSO and for 1 month after the last dose. Advise male patients with female partners of reproductive potential to use effective contraception during treatment with MODEYSO and for 1 month after the last dose [see Use in Specific Populations (8.1, 8.3)].

6 ADVERSE REACTIONS

The following potential clinically significant adverse reactions are described elsewhere in the labelling:

- Hypersensitivity [see Warnings and Precautions (5.1)].
- QTc Interval Prolongation [see Warnings and Precautions (5.2)].

6.1 Clinical Trials Experience

Because clinical trials are conducted under widely varying conditions, adverse reaction rates observed in the clinical trials of a drug cannot be directly compared to rates in the clinical trials of another drug and may not reflect the rates observed in practice.

The pooled safety population described in WARNINGS AND PRECAUTIONS and below reflects exposure to MODEYSO at the recommended weight-based dose taken until disease progression or unacceptable toxicity in 376 adult and pediatric patients with glioma across four open-label clinical studies (ONC006, ONC013, ONC014, and ONC018) [see Clinical Studies (14)].

Of the 376 patients who received MODEYSO, 35% were exposed for 6 months, and 17% were exposed for 1 year.

The median age was 23 years (range: 3 to 80): 30% were 2 to 11 years old, 11% were 12 to 17 years old, 55% were 18 to 64 years old, and 3.7% were 65 years or older. Fifty-two percent (52%) were female; 74% White, 10% unknown race or race not reported, 9% Black or African American, 4% Asian, 2.9% other or multiple races; and 13% were of Hispanic or Latino ethnicity. Karnofsky/Lansky Performance Status (KPS/LPS) score was 80 to 100 in 66% of patients, 60 to 70 in 27%, and <60 in 7%.

Relevant disease characteristics included primary tumor locations in the midline (91%) and non‑midline regions (9%); 33% had diffuse intrinsic pontine glioma (DIPG); 30% had multifocal disease; 79% had an H3 K27M mutation; 75% had recurrent disease.

Serious adverse reactions occurred in 33% of patients who received MODEYSO. Serious adverse reactions in >2% of patients included hydrocephalus (5%), vomiting (4.3%), headache (3.2%), seizure (2.4%), and muscular weakness (2.1%). Fatal adverse reactions occurred in 1% of patients who received MODEYSO, including cardiac arrest (0.5%), intracranial hemorrhage (0.3%), and encephalopathy (0.3%).

Permanent discontinuation of MODEYSO due to an adverse reaction occurred in 2.1% of patients. Adverse reactions which resulted in permanent discontinuation of MODEYSO in >1 patient included confusional state.

Dosage interruptions of MODEYSO due to an adverse reaction occurred in 6% of patients. Adverse reactions which required dosage interruption in >1 patient included increased alanine aminotransferase, increased aspartate aminotransferase, decreased lymphocyte count, muscular weakness, and aspiration pneumonia.

Dose reductions of MODEYSO due to an adverse reaction occurred in 2.7% of patients. Adverse reactions which required dose reductions in >1 patient included decreased neutrophil count and increased alanine aminotransferase.

The most common adverse reactions (≥20%) were fatigue, headache, vomiting, nausea, and musculoskeletal pain. The most common (≥2%) Grade 3 or 4 laboratory abnormalities were decreased lymphocytes, decreased calcium, and increased alanine aminotransferase.

Adverse reactions that occurred in at least 10% of patients treated with MODEYSO are presented in Table 4.

Table 4: Adverse Reactions (≥10%) in Patients with Glioma Who Received MODEYSO in ONC006, ONC013, ONC014, and ONC018
Adverse Reaction | MODEYSO; (N=376)
Adverse Reaction | All Grades (%) | Grade 3 or 4 (%)
General Disorders
Fatiguea | 34 | 3.2
Gait disturbance | 16 | 3.7
Nervous System Disorders
Headacheb | 32 | 4.3
Cranial nerve disordersc | 16 | 1.3
Hemiparesis | 15 | 4.5
Dysarthria | 13 | 2.7
Dizziness | 13 | 0.5
Ataxia | 10 | 1.3
Gastrointestinal Disorders
Vomiting | 24 | 2.7
Nausea | 24 | 0.8
Dysphagia | 13 | 2.1
Constipation | 11 | 0
Musculoskeletal and Connective Tissue Disorders
Musculoskeletal paind | 20 | 2.9
Muscular weakness | 13 | 4.5
Metabolism and Nutrition Disorders
Hyperglycemia | 12 | 0.8
Infections and Infestations
Rashe | 11 | 0.8

a. Includes asthenia.

b. Includes head discomfort and sinus headache.

c. Includes accessory nerve disorder, auditory nerve disorder, facial nerve disorder, facial paralysis, facial paresis, glossopharyngeal nerve disorder, hypoglossal nerve disorder, IIIrd nerve disorder, IIIrd nerve paralysis, IVth nerve disorder, IVth nerve paralysis, tongue paralysis, trigeminal nerve disorder, trigeminal neuralgia, VIth nerve disorder, VIth nerve paralysis, and VIth nerve paresis.

d. Includes back pain, pain in extremity, arthralgia, neck pain, non-cardiac chest pain, myalgia, bone pain, musculoskeletal chest pain, musculoskeletal stiffness, and spinal pain.

e. Includes dermatitis, dermatitis acneiform, dermatitis bullous, eczema, erythema multiforme, rash erythematous, rash macular, rash maculo-papular, rash papular, rash pruritic, and rash pustular.

Other clinically important adverse reactions observed in less than 10% of patients treated with MODEYSO were peripheral neuropathy, seizure, diarrhea, tremor, and venous thromboembolic events.

Selected laboratory abnormalities that occurred in at least 10% of patients treated with MODEYSO are presented in Table 5.

Table 5: Select Laboratory Abnormalities (≥10%) that Worsened from Baseline in Patients with Glioma Receiving MODEYSO in ONC006, ONC013, ONC014, and ONC018
Laboratory Abnormalitya | MODEYSOb
Laboratory Abnormalitya | All Grades (%) | Grade 3 or 4 (%)
Chemistry
Alanine aminotransferase increased | 28 | 2.4
Aspartate aminotransferase increased | 22 | 0.9
Calcium decreased | 20 | 2.7
Sodium decreased | 14 | 0.3
Potassium decreased | 13 | 0.3
Glucose decreased | 11 | 0
Alkaline phosphatase increased | 11 | 0.3
Hematology
Hemoglobin decreased | 25 | 0.6
Neutrophils decreased | 24 | 1.5
Lymphocytes decreased | 19 | 7

a. Severity as defined by the National Cancer Institute CTCAE Version 5.0.

b. The denominator for each laboratory parameter is based on the number of patients with a baseline and post‑treatment laboratory value available, which ranged from 325 to 330 patients.

7 DRUG INTERACTIONS

7.1 Effect of Other Drugs on MODEYSO

Table 6 describes drug interactions where concomitant use of another drug affects MODEYSO.

Table 6: Effect of Other Drugs on MODEYSO
Strong and Moderate CYP3A4 Inhibitors
Prevention or Management | - Avoid concomitant use of strong and moderate CYP3A4 inhibitors with MODEYSO. - If concomitant use cannot be avoided for adults and pediatric patients who weigh at least 52.5 kg, reduce the MODEYSO dose as recommended [see Dosage and Administration (2.5)].
Mechanism and Clinical Effects | - Dordaviprone is a CYP3A4 substrate. - Strong and moderate CYP3A4 inhibitors increase dordaviprone exposure [see Clinical Pharmacology (12.3)], which may increase the risk of MODEYSO‑related adverse reactions [see Warnings and Precautions (5.2)].
Strong or Moderate CYP3A4 Inducers
Prevention or Management | - Avoid concomitant use of strong and moderate CYP3A4 inducers with MODEYSO.
Mechanism and Clinical Effects | - Dordaviprone is a CYP3A4 substrate. - Strong and moderate CYP3A4 inducers decrease dordaviprone exposure [see Clinical Pharmacology (12.3)], which may reduce the anti-tumor activity of MODEYSO.

7.2 Drugs Known to Prolong QTc Interval

Table 7 describes drug interactions associated with QTc interval prolongation when used concomitantly with MODEYSO.

Table 7: Products that Prolong QTc Interval
Products that Prolong QTc Interval
Prevention or Management | - Avoid concomitant use of MODEYSO with products known to prolong the QTc interval. - If concomitant use cannot be avoided, separate administration of MODEYSO and the QT-prolonging product [see Warnings and Precautions (5.2) and Clinical Pharmacology (12.2)].
Clinical Impact | - MODEYSO causes concentration dependent QTc interval prolongation [see Clinical Pharmacology (12.2)]. - Concomitant use of MODEYSO with other QT-prolonging products may increase the risk of QTc-associated arrhythmias [see Warnings and Precautions (5.2)].

8 USE IN SPECIFIC POPULATIONS

8.1 Pregnancy

Risk Summary

Based on findings from animal studies and its mechanism of action [see Clinical Pharmacology (12.1)], MODEYSO can cause fetal harm when administered to a pregnant woman. There are no available data on MODEYSO use in pregnant women to inform a drug‑associated risk.

In animal embryo-fetal development studies, oral administration of dordaviprone to pregnant rats and rabbits during the period of organogenesis caused embryofetal mortality, alterations to growth, and structural abnormalities at exposures below the human exposure at the highest recommended dose (see Data). Advise pregnant women of the potential risk to a fetus.

In the U.S. general population, the estimated background risk of major birth defects and miscarriage in clinically recognized pregnancies is 2% to 4% and 15% to 20%, respectively.

Data

Animal Data

In an embryo-fetal development study, dordaviprone was administered orally to pregnant rats during the period of organogenesis from gestation day 7 to 17 at doses of 25, 62.5, and 125 mg/kg/day. Dordaviprone caused maternal mortality, pre-implantation loss, and embryo-fetal toxicity of absent eye and small renal papillae at the 125 mg/kg/day dose (≥2 times the human recommended doses based on body surface area). In an embryo-fetal development study, dordaviprone was administered orally to pregnant rabbits during the period of organogenesis from gestation days 7 to 19 at doses of 10, 25, 62.5, and 100 mg/kg/day. Dordaviprone caused maternal mortality, embryo‑fetal mortality, lower fetal weights, and structural malformations of the face, limbs, vessels, brain, and heart at doses of ≥10 mg/kg/day (≥0.4 times the human exposure at the highest recommended dose based on Cmax).

8.2 Lactation

Risk Summary

There are no data on the presence of dordaviprone or its metabolites in human milk, their effects on a breastfed child, or on milk production. Because of the potential for serious adverse reactions in breastfed children from MODEYSO, advise women not to breastfeed during treatment with MODEYSO and for 1 week after the last dose.

8.3 Females and Males of Reproductive Potential

MODEYSO can cause fetal harm when administered to a pregnant woman [see Use in Specific Populations (8.1)].

Pregnancy Testing

Verify pregnancy status of females of reproductive potential prior to initiating MODEYSO [see Use in Specific Populations (8.1)].

Contraception

Females

Advise females of reproductive potential to use effective contraception during treatment with MODEYSO and for 1 month after the last dose [see Use in Specific Populations (8.1)].

Males

Advise male patients with female partners of reproductive potential to use effective contraception during treatment with MODEYSO and for 1 month after the last dose.

Infertility

Based on the mechanism of action of dordaviprone (dopamine D2 receptor inhibition and alterations to mitochondrial function), treatment with MODEYSO may adversely impact fertility in males and females.

8.4 Pediatric Use

The safety and effectiveness of MODEYSO has been established in pediatric patients aged 1 year and older for the treatment of diffuse midline glioma harboring an H3 K27M mutation [see Adverse Reactions (6.1) and Clinical Studies (14)].

The efficacy of MODEYSO was evaluated in 4 pediatric patients aged 9 to 17 years with diffuse midline glioma harboring an H3 K27M mutation. Safety was evaluated in 154 pediatric patients with glioma aged 3 to 17 years who received MODEYSO at the recommended dose across four open‑label clinical studies (ONC006, ONC013, ONC014, and ONC018). Of these 154 patients, 73% were 3 to 11 years of age and 27% were 12 to 17 years of age. No additional safety signals were observed in pediatric patients [see Adverse Reactions (6.1)].

The exposure of dordaviprone in pediatric patients weighing 10 kg and higher is predicted to be within the range of exposures predicted in adults at the recommended dosage [see Clinical Pharmacology (12.3)].

The safety and effectiveness of MODEYSO have not been established in pediatric patients less than 1 year of age.

8.5 Geriatric Use

Of the 376 patients with glioma who received MODEYSO at the recommended dose across four open-label clinical studies (ONC006, ONC013, ONC014, and ONC018), 3.7% of patients were ≥65 years of age and 0.5% were ≥75 years of age. Clinical studies of MODEYSO did not include sufficient numbers of patients aged 65 and over to determine whether they respond differently than younger patients.

11 DESCRIPTION

Dordaviprone is a protease activator.

Dordaviprone is present as dordaviprone hydrochloride with the molecular formula C24H26N4O•2HCl. The molecular weight is 459.41. The full chemical name for dordaviprone hydrochloride is 7-benzyl-4-(2-methylbenzyl)-1,2,6,7,8,9-hexahydroimidazo[1,2-a]pyrido[3,4-e]pyrimidin-5(4H)-one dihydrochloride.

Dordaviprone hydrochloride has the following chemical structure:

Dordaviprone hydrochloride is a white to off-white solid that is freely soluble in water. The 1% solution of dordaviprone hydrochloride is measured as pH 3.3.

MODEYSO (dordaviprone) capsules are supplied as 125 mg strength capsules in an immediate‑release oral formulation. Each MODEYSO capsule contains 125 mg of dordaviprone (equivalent to 148.8 mg of dordaviprone hydrochloride).

The inactive ingredients in the capsule include magnesium stearate, microcrystalline cellulose, and sodium starch glycolate. The capsule shell consists of hypromellose and titanium dioxide. The black printing ink contains alcohol, D&C yellow #10, FD&C blue #1, FD&C blue #2, FD&C red #40, ferrosoferric oxide, methyl alcohol, N‑butyl alcohol, propylene glycol, and shellac glaze (20% esterified).

12 CLINICAL PHARMACOLOGY

12.1 Mechanism of Action

Dordaviprone is a protease activator of the mitochondrial caseinolytic protease P (ClpP). Dordaviprone also inhibits the dopamine D2 receptor.

Diffuse midline gliomas harboring an H3 K27M mutation are associated with the loss of H3 K27 trimethylation. In-vitro, dordaviprone activated the integrated stress response, induced apoptosis, and altered mitochondrial metabolism leading to restored histone H3 K27 trimethylation in H3 K27M-mutant diffuse glioma models.

Dordaviprone exhibited antitumor activity in cell-based assays and in vivo models of H3 K27M-mutant diffuse glioma.

12.2 Pharmacodynamics

Cardiac Electrophysiology

At 1.2 times the maximum recommended dose, the estimated mean QTcF change was 11.8 msec (90% CI: 9.8, 13.7) [see Warnings and Precautions (5.2) and Drug Interactions (7.2)].

Pharmacodynamics

The exposure-response relationship and time course of pharmacodynamic response for the safety and effectiveness of dordaviprone have not been fully characterized.

12.3 Pharmacokinetics

Dordaviprone pharmacokinetics were predicted following a single dose in patients at the approved recommended dosage and are presented as mean (CV%) unless otherwise specified. Dordaviprone maximum concentration (Cmax) is 2.8 mcg/mL (42%), and total systemic exposure (AUC) is 23 hr·mcg/mL (48%). Dordaviprone Cmax and AUC increased in a dose proportional manner over the dose range of 125 to 625 mg. No accumulation is observed following once weekly dosing.

Absorption

Dordaviprone median (min, max) time to maximum plasma concentration (Tmax) is 1.4 hours (0.5, 5.6 hours).

Food Effect

Dordaviprone Cmax decreased by 40% with no change on AUC following administration with a high-fat meal (800 to 1,000 calories, 50% fat).

Distribution

Dordaviprone apparent (oral) volume of distribution is 450 L (40%).

Dordaviprone plasma protein binding is 95% to 97% and independent of concentrations in vitro.

The median blood-to-plasma ratio is 0.67 in vitro.

Metabolism

Dordaviprone is primarily metabolized by CYP3A4 with minor contribution from CYP2B6, CYP2C8, CYP2C9, CYP2D6, and CYP3A5.

Excretion

Dordaviprone mean terminal half-life is 11 hours (30%), and the apparent clearance is approximately 27 L/hr (48%).

Following a single dose of radiolabeled dordaviprone, 70% of the dose was recovered in urine and 20% in feces with no notable unchanged dordaviprone in urine or feces.

Specific Populations

No clinically significant differences in the pharmacokinetics of dordaviprone were observed based on age (3 to 90 years), sex, race (74% White, 9% Black or African American, or 5% Asian) or mild hepatic impairment (total bilirubin ≤ULN with AST >ULN or total bilirubin >1 to 1.5 times ULN with any AST).

The effect of severe hepatic impairment (total bilirubin >3 times ULN with any AST) on dordaviprone pharmacokinetics is unknown.

Pediatric Patients

The exposure of dordaviprone in pediatrics weighing 10 kg and higher is predicted to be within the range of exposures predicted in adults at the recommended dosage.

Renal Impairment

Following a single oral dose of 375 mg (0.6 times the maximum approved recommended dose), dordaviprone AUC increased by 1.5-fold and Cmax by 1.1-fold in subjects with severe renal impairment (CLcr <30 mL/min, estimated by the Cockcroft-Gault equation).

Hepatic Impairment

Following a single oral dose of 125 mg (0.2 times the maximum approved recommended dose) dordaviprone AUC increased by 1.5-fold and Cmax by 1.2-fold in subjects with moderate hepatic impairment (Child Pugh class B).

Drug Interaction Studies

Clinical Studies and Model-Informed Approaches

CYP3A4 Inhibitors: Dordaviprone Cmax increased by 2-fold and AUC increased by 4-fold following concomitant administration of itraconazole (strong CYP3A4 inhibitor) 200 mg once daily for 8 days.

Dordaviprone Cmax is predicted to increase by ~1.5-fold and AUC by 2.5-fold following concomitant administration of fluconazole or erythromycin (moderate CYP3A4 inhibitor).

CYP3A4 Inducers: Dordaviprone Cmax is predicted to decrease by 68% and AUC by 83% following concomitant administration of rifampin (strong CYP3A4 inducer) and dordaviprone Cmax is predicted to decrease by 44% and AUC by 65% following concomitant administration of efavirenz (moderate CYP3A4 inducer).

Other Drugs: No clinically significant difference in dordaviprone pharmacokinetics is predicted when used concomitantly with cimetidine (weak CYP3A4 inhibitor).

No clinically significant difference in dordaviprone pharmacokinetics is observed with multiple doses of a rabeprazole (proton-pump inhibitor).

No clinically significant differences in the pharmacokinetics of the following drugs are predicted following concomitant use with MODEYSO: dabigatran etixelate (P-gp substrate), rosuvastatin (BCRP substrate), midazolam (CYP3A substrate), desipramine (CYP2D6 substrate) and repaglinide (CYP2C8 substrate).

In Vitro Studies

CYP Enzymes: Dordaviprone inhibits CYP1A2, CYP2B6, and CYP2C19 and induces CYP2B6.

Transporter Systems: Dordaviprone inhibits MATE1, MATE2-K, OAT1, OAT3, OATP1B1, OATP1B3, and OCT1.

13 NONCLINICAL TOXICOLOGY

13.1 Carcinogenesis, Mutagenesis, Impairment of Fertility

Carcinogenesis

Carcinogenicity studies with dordaviprone were not conducted.

Mutagenesis

Dordaviprone was not genotoxic in in vitro (Ames and micronucleus assay) and in vivo (mouse micronucleus) assays.

Impairment of Fertility

Dedicated fertility studies were not conducted with dordaviprone.

13.2 Animal Toxicology and/or Pharmacology

The nonclinical safety profile of dordaviprone reflects the on-target pharmacology and dopamine receptor inhibition. In repeat-dose toxicology studies of up 13 weeks in duration, weekly oral administration of dordaviprone to dogs caused central nervous system-related toxicities including whole body tremors, cranial tremors, seizures, excessive salivation, lateral recumbency, rigidity, paddling of limbs, overall rigid body, salivation, abnormal gait/stance, and twitching at doses resulting in less than or equal to 0.7 times the human exposure at the highest recommended dose based on AUC. In a 13-week repeat-dose toxicology study in rats, mammary gland hyperplasia occurred at doses resulting in 0.11 times the human exposure at the highest recommended dose based on AUC.

14 CLINICAL STUDIES

The efficacy of MODEYSO was evaluated in adult and pediatric patients with glioma across five open‑label, non-randomized clinical studies conducted in the U.S. (ONC006 [NCT02525692], ONC013 [NCT03295396], ONC014 [NCT03416530], ONC016 [NCT05392374], and ONC018 [NCT03134131]). Pre-specified criteria were defined to establish an integrated efficacy population; eligible patients were required to have received single-agent MODEYSO, have diffuse midline glioma harboring an H3 K27M mutation with progressive and measurable disease per Response Assessment in Neuro-Oncology-High Grade Glioma (RANO-HGG) criteria, be ≥90 days post‑radiation therapy, have adequate washout from prior anticancer therapies, have a Karnofsky Performance Status/Lansky Performance Status (KPS/LPS) score ≥60, and have stable or decreasing corticosteroid use. Patients with diffuse intrinsic pontine glioma (DIPG), primary spinal tumors, atypical histologies, or cerebrospinal fluid dissemination were excluded. Patients received weight-based dosing of MODEYSO until disease progression or unacceptable toxicity.

The integrated efficacy population included 50 patients who met these criteria. The major efficacy outcome measure was overall response rate (ORR) assessed by blinded independent central review (BICR) according to RANO 2.0 criteria. Additional efficacy outcome measures were BICR-assessed ORR according to RANO-HGG criteria and Response Assessment in Neuro-Oncology-Low Grade Glioma (RANO-LGG) criteria, duration of response, and time to response.

Baseline demographics were: median age 31 years (range: 9 to 70) with 6% younger than 17 years of age; 46% female; 80% White, 6% Black or African American, 2% Asian, 10% other races, and 2% race unknown; 8% were of Hispanic or Latino ethnicity; 72% had KPS/LPS 80 to 100. Relevant disease characteristics included 72% treated at first recurrence, 28% had 2 or more recurrences; primary tumor location was thalamic in 52% and non-thalamic midline region in 48%; 88% received prior temozolomide; 62% were receiving corticosteroids at baseline; median time from end of prior radiation was 7.4 months (range: 3.0 to 102.1).

Efficacy results are shown in Table 8.

Table 8: Efficacy Results for Patients with Diffuse Midline Glioma Harboring an H3 K27M Mutation in Studies ONC006, ONC013, ONC014, ONC016, and ONC018 per RANO 2.0
Efficacy Parameter | MODEYSO; N=50
Overall Response Rate (95% CI)a | 22% (12, 36)
Partial response (PR) | 16%
Minor response (MR) | 6%
Duration of Response | N=11
Median (95% CI)b, months | 10.3 (7.3, 15.2)
% with observed DOR ≥6 monthsc | 73%
% with observed DOR ≥12 monthsc | 27%

Abbreviations: BICR=blinded independent central review; CI=confidence interval; RANO=Response Assessment in Neuro-Oncology.

a. Confirmed overall response rate assessed by BICR; CI based on Clopper-Pearson method.

b. Based on Kaplan-Meier estimate.

c. Based on observed time.

Among responders, the median time to response was 3.6 months (range 1.6, 15.6).

Using BICR-assessed RANO 2.0 criteria, there was one additional responder based on the integrated response assessment, which takes into account corticosteroid use and performance status. Based on BICR-assessed RANO-HGG criteria (n=50), the ORR was 20% (95% CI: 10, 34), with 1 complete and 9 partial responses. Based on BICR-assessed RANO-LGG criteria (n=50), the ORR was 20% (95% CI: 10, 34), with 5 partial and 5 minor responses.

16 HOW SUPPLIED/STORAGE AND HANDLING

How Supplied

Strength | Description | Package Configuration | NDC Number
125 mg | White, opaque, hard capsules printed with “DDP” and “125” on the body and “CMRX” on the cap of the capsule. | Each bottle contains 10 capsules and desiccant with a child‑resistant closure. | 68727-250-01

Storage

Store at 20°C to 25°C (68°F to 77°F); excursions permitted from 15°C to 30°C (59°F to 86°F) [see USP Controlled Room Temperature].

17 PATIENT COUNSELING INFORMATION

Advise the patient and caregiver to read the FDA-approved patient labeling (Patient Information and Instructions for Use).

Hypersensitivity

Advise patients that MODEYSO can cause hypersensitivity. Inform patients about the signs and symptoms of hypersensitivity reactions and instruct patients or caregivers to seek immediate medical attention if symptoms occur [see Warnings and Precautions (5.1)].

QTc Interval Prolongation

Advise patients that MODEYSO can cause QTc interval prolongation. Inform patients of the signs and symptoms of QTc prolongation and instruct patients or caregivers to seek immediate medical attention if symptoms occur [see Warnings and Precautions (5.2)].

Drug Interactions

Inform patients that MODEYSO may interact with some drugs. Advise patients to inform their healthcare provider about all medications they are taking, including prescription and over-the-counter drugs, vitamins, and herbal products. Additionally, patients should consult their healthcare provider before starting or stopping any prescription drug, nonprescription drug, or supplement [see Drug Interactions (7)].

Administration

Instruct patients and caregivers to read the Instructions for Use before taking MODEYSO, and each time the patient gets a refill as there may be new information they need to know.

Patients should take MODEYSO orally once weekly on an empty stomach (no food intake at least 1 hour prior to or 3 hours after taking MODEYSO). Take the prescribed dose at the same time on the same day of the week [see Dosage and Administration (2.3) and Clinical Pharmacology (12.3)].

Instruct patients to swallow capsules whole. For patients unable to swallow capsules whole, instruct patients to open capsules and mix contents with approximately 15 to 30 mL of liquid (sports drink, apple juice, lemonade, or water). Instruct patients to drink the mixture. After drinking the mixture, instruct patients to add another 15 to 30 mL of the liquid to the container, swirl to dissolve any remaining medication, and then drink the remaining contents [see Dosage and Administration (2.3) and Instructions for Use].

Embryo-fetal Toxicity

Advise pregnant women and females of reproductive potential of the potential risk to a fetus.

Advise females to inform their healthcare provider of a known or suspected pregnancy [see Warnings and Precautions (5.3) and Use in Specific Populations (8.1, 8.3)].

Advise females of reproductive potential to use effective contraception during treatment with MODEYSO and for 1 month after the last dose [see Use in Specific Populations (8.3)].

Advise male patients with female partners of reproductive potential to use effective contraception during treatment with MODEYSO and for 1 month after the last dose [see Use in Specific Populations (8.3)].

Lactation

Advise women not to breastfeed during treatment with MODEYSO and for 1 week after the last dose [see Use in Specific Populations (8.2)].

Distributed by:

Jazz Pharmaceuticals, Inc.

Palo Alto, CA 94306

Patient Package Insert

PATIENT INFORMATION

MODEYSO (moh-DAY-soh)

(dordaviprone)

capsules, for oral use

What is MODEYSO?

MODEYSO is a prescription medicine used to treat adults and children 1 year of age and older with a certain type of brain tumor called diffuse midline glioma that has a specific “H3 K27M” gene mutation and has worsened after other treatments.

It is not known if MODEYSO is safe and effective in children less than 1 year of age.

Before taking MODEYSO, tell your healthcare provider about all your medical conditions, including if you:

- have heart failure or heart rhythm problems, including QT prolongation and long QT syndrome.
- are pregnant or plan to become pregnant. MODEYSO can harm your unborn baby. Tell your healthcare provider right away if you become pregnant or think that you may be pregnant during treatment with MODEYSO.
  - Your healthcare provider should check to see if you are pregnant before you begin treatment with MODEYSO.
  - Females who are able to become pregnant should use effective birth control (contraception) during treatment with MODEYSO and for 1 month after your last dose.
  - Males with partners who are able to become pregnant should use effective contraception during treatment with MODEYSO and for 1 month after your last dose.
- are breastfeeding or plan to breastfeed. It is not known if MODEYSO passes into breast milk. Do not breastfeed during treatment with MODEYSO and for 1 week after your last dose. Talk to your healthcare provider about the best way to feed your baby during this time.

Tell your healthcare provider about all the medicines you take, including prescription and over-the-counter medicines, vitamins, and herbal supplements. MODEYSO and other medicines may affect the way each other work and may cause serious side effects. You can ask your healthcare provider or pharmacist for a list of medications that interact with MODEYSO.

Know the medicines you take. Keep a list of your medicines to show your healthcare provider and pharmacist. Do not start or stop taking any new medicines without first talking to your healthcare provider.

How should I take MODEYSO?

- Take MODEYSO exactly as your healthcare provider tells you.
- Do not change your dose or stop taking MODEYSO without talking to your healthcare provider.
- Your healthcare provider may change your dose, temporarily stop, or completely stop treatment with MODEYSO if you develop certain side effects.
- Take MODEYSO 1 time each week on the same day of the week. Take all of the capsules prescribed for your dose at the same time.
- Take MODEYSO on an empty stomach, at least 1 hour before or 3 hours after eating food.
- Swallow MODEYSO capsules whole. If the capsules cannot be swallowed whole, see the detailed Instructions for Use for how to prepare and take or give MODEYSO as a liquid.
- If vomiting happens after taking a dose of MODEYSO, do not take another dose. Take the next dose of MODEYSO on the next regularly scheduled weekly day of the week.
- If you miss a weekly dose of MODEYSO by:
  - 2 days or less, take the missed dose as soon as you remember. Take the next dose of MODEYSO on the next regularly scheduled day of the week.
  - More than 2 days, skip the missed dose and take the next dose of MODEYSO on the next regularly scheduled day of the week.

What are the possible side effects of MODEYSO?

MODEYSO may cause serious side effects, including:

- Allergic reactions. Allergic reactions may happen during treatment with MODEYSO and can be severe. Stop taking MODEYSO and get immediate emergency medical help right away if you get any signs or symptoms of allergic reactions, including:
  - rash
  - hives
  - fever
  - feeling faint or dizzy
  - wheezing or trouble breathing
  - swelling of the face or throat
- Heart rhythm problems (QTc interval prolongation). MODEYSO can cause changes in the electrical activity of your heart and can increase your chance of getting a type of abnormal heart rhythm that can lead to sudden death called torsades de pointes. Before you start treatment and during treatment as needed, your healthcare provider will check your heart using an electrocardiograph (ECG) and check your blood levels of salts called electrolytes. Get emergency medical help right away if you get any signs or symptoms of abnormal heart rhythm, including:
  - feeling lightheaded or faint
  - dizziness
  - fast heartbeat
  - heart palpitations
  - shortness of breath

The most common side effects of MODEYSO include:

- tiredness
- headache
- vomiting
- nausea
- muscle, joint, and bone pain

The most common abnormal blood tests include decreased white blood cells, decreased red blood cells, decreased calcium, and increased liver enzymes.

MODEYSO may cause fertility problems in males and females, which may affect your ability to have children. Talk to your healthcare provider if this is a concern for you.

These are not all of the possible side effects of MODEYSO. Call your doctor for medical advice about side effects. You may report side effects to FDA at 1‑800‑FDA-1088.

You may also report side effects to Chimerix, Inc. at 1-866-662-2679.

How should I store MODEYSO?

- Store MODEYSO at room temperature between 68°F to 77°F (20°C to 25°C).
- The MODEYSO bottle has a child-resistant closure.

Keep MODEYSO and all medicines out of the reach of children.

General information about the safe and effective use of MODEYSO.

Medicines are sometimes prescribed for purposes other than those listed in a Patient Information leaflet. Do not use MODEYSO for a condition for which it was not prescribed. Do not give MODEYSO to other people, even if they have the same symptoms that you have. It may harm them. You can ask your pharmacist or healthcare provider for information about MODEYSO that is written for health professionals.

What are the ingredients in MODEYSO?

Active ingredient: dordaviprone

Inactive ingredients: magnesium stearate, microcrystalline cellulose, and sodium starch glycolate. The capsule shell contains hypromellose and titanium dioxide. The black printing ink contains alcohol, D&C yellow #10, FD&C blue #1, FD&C blue #2, FD&C red #40, ferrosoferric oxide, methyl alcohol, N-butyl alcohol, propylene glycol, and shellac glaze (20% esterified).

Distributed by:

Jazz Pharmaceuticals, Inc.

Palo Alto, CA 94306

For more information, contact Chimerix, Inc. at 1-866-662-2679.

This Patient Information has been approved by the U.S. Food and Drug Administration. Issued: 08/2025

Instructions for Use

MODEYSO [moh-DAY-soh]

(dordaviprone)

capsules, for oral use

This Instructions for Use contains information on how to prepare and take or give MODEYSO capsules as a liquid.

Read this Instructions for Use carefully before you prepare and take or give a dose of MODEYSO for the first time and each time you or your child gets a prescription refill. There may be new information. This information does not take the place of talking with your healthcare provider about your or your child’s medical condition or treatment.

Important Information You Need to Know Before Preparing and Taking or Giving MODEYSO Capsules as a Liquid.

- For oral use only (take by mouth).
- Take or give MODEYSO exactly as your healthcare provider tells you. Do not change the dose or stop taking MODEYSO without talking to your healthcare provider.
- Take or give MODEYSO 1 time each week on the same day of the week. Take or give all of the capsules prescribed for your dose at the same time.
- Take or give MODEYSO on an empty stomach, at least 1 hour before or 3 hours after eating food.
- If you or your child cannot swallow the capsules whole, the capsules can be dissolved in sports drink, apple juice, lemonade, or water and taken as a liquid.
- Check the expiration date on the MODEYSO bottle. Do not take or give MODEYSO if the expiration date has passed. Contact your pharmacist if the medicine is expired.
- Do not take or give MODEYSO if the bottle or the capsules are broken or damaged. Contact your healthcare provider or pharmacist for a replacement.

Supplies needed to prepare and dissolve MODEYSO capsules to take or give as a liquid.

Section A: Preparing and dissolving MODEYSO capsules to take or give as a liquid

Preparing to dissolve the capsules

Step 1:

Wash and dry your hands.

Place the MODEYSO bottle on a clean, flat surface.

Gather the rest of the supplies you will need so they are ready to use.

Step 2:

Check the prescribed dose. Count out the number of MODEYSO capsules needed for the dose.

Opening the capsules

Step 3:

Hold the capsule over a clean, empty cup.

Carefully open the capsule by gently pulling and twisting both ends.

Slowly empty the contents (powder) into the cup.

If any powder remains inside the capsule shell, gently tap the shell over the cup to remove any remaining powder.

Step 4:

Repeat Step 3 for each additional capsule needed for the prescribed dose.

Dissolving the capsules in liquid

Step 5:

Use a tablespoon (15 mL) to measure the liquid.

Add 1 to 2 tablespoons (about 15 mL to 30 mL) of your chosen liquid (sports drink, apple juice, lemonade, or water) to the cup.

Step 6:

Gently swirl the liquid around the cup before taking or giving the mixture until no large chunks of powder remain. The mixture may look cloudy. This is normal and okay.

Section B: Taking or giving a dose of MODEYSO as a liquid

Step 7:

Take or give all of the mixture as soon as possible. Always take or give the mixture within 2 hours of preparing it.

An oral dosing syringe may be used to take or give the mixture by mouth. Refer to Section D for detailed instructions.

The mixture may be taken or given through a feeding tube. Refer to Section E for detailed instructions.

Throw away the mixture if it is not taken within 2 hours of preparing it and go back to Section A to prepare a new dose.

If vomiting happens after taking or giving the dose, or not all of the liquid is swallowed, do not take or give another dose. Take the next dose of MODEYSO on the next regularly scheduled day of the week.

Step 8:

After taking or giving the dose, add 1 to 2 more tablespoons (about 15 mL to 30 mL) of your chosen liquid to the cup.

Step 9:

Swirl the liquid around the cup to make sure any remaining medicine is mixed with the liquid.

This helps make sure that no medicine is left behind.

Step 10:

Repeat Step 7.

Section C: Disposing of (throwing away) empty MODEYSO capsule shells and cleaning the cup

Step 11:

After taking or giving the dose, throw empty capsule shells in the trash.

Do not save or reuse empty capsules.

Step 12:

After taking or giving the dose, rinse the cup with warm running water to remove all remaining medicine.

Step 13:

Wash your hands with soap and water.

Section D: Taking or giving a dose of MODEYSO as a liquid using an oral dosing syringe

If you are using an oral dosing syringe to take or give MODEYSO by mouth:

1. Follow Steps 1 through 6 in Section A to prepare the MODEYSO liquid mixture in a cup.
2. If there is a cap, remove the cap of the oral dosing syringe.
3. Push the plunger down into the oral dosing syringe as far as it will go.
4. Place the oral dosing syringe tip in the mixture in the cup. Pull up on the plunger to draw all the mixture into the oral dosing syringe.
5. You or your child should sit upright to take or give a dose of MODEYSO. Place the tip of the oral dosing syringe towards the inside of the cheek in your or your child’s mouth.
6. Slowly push the medicine into the mouth by pressing down on the plunger, allowing time for swallowing. Do not forcefully push the plunger. This may cause choking.
7. You or your child may drink other liquids right away after swallowing the mixture.
8. Steps 3 through 7 in this section may be repeated until all the mixture has been taken or given.
9. After taking or giving the dose, add 1 to 2 more tablespoons (about 15 mL to 30 mL) of your chosen liquid to the cup.
10. Swirl the liquid around the cup to make sure any remaining medicine is mixed with the liquid. This helps make sure that no medicine is left behind.
11. Using the oral dosing syringe, repeat Steps 3 through 6 in this section until all of the mixture in the cup has been taken or given.
12. After completing Step 11 in this section, remove the plunger from the oral dosing syringe and rinse each part with warm running water to remove all remaining medicine. Allow the parts to air dry completely before putting the syringe back together.

Refer to Section C: Disposing of (throwing away) empty MODEYSO capsule shells and cleaning the cup.

Section E: Taking or giving a dose of MODEYSO as a liquid using a feeding tube

MODEYSO may be given through a naso-gastric (“ng”) or gastrostomy (“g”) feeding tube, as directed by your healthcare provider.

1. Follow Steps 1 through 6 in Section A to prepare the MODEYSO liquid mixture in a cup.
2. Flush the feeding tube according to the manufacturer's instructions before each dose.
3. Draw up the mixture into a catheter tip syringe.
4. Connect the syringe containing the mixture to the feeding tube.
5. Apply slow, steady pressure to the plunger to give all the contents of the syringe through the feeding tube.
6. After giving the dose, add 1 to 2 more tablespoons (about 15 mL to 30 mL) of your chosen liquid to the cup.
7. Swirl the liquid around the cup to make sure any remaining medicine is mixed with the liquid. This helps make sure that no medicine is left behind.
8. Using the syringe, repeat Steps 3 through 5 in this section until all the mixture in the cup has been given.
9. After completing Step 8 in this section, flush the feeding tube according to the manufacturer's instructions.
10. After completing Step 9 in this section, remove the plunger from the syringe and rinse each part with warm running water to remove all remaining medicine. Allow the parts to air dry completely before putting the syringe back together.

Refer to Section C: Disposing of (throwing away) empty MODEYSO capsule shells and cleaning the cup.

Storing MODEYSO

- Store MODEYSO at room temperature between 68°F to 77°F (20°C to 25°C).
- The MODEYSO bottle has a child-resistant closure.

Keep MODEYSO and all medicines out of the reach of children.

Distributed by:
Jazz Pharmaceuticals, Inc.
Palo Alto, CA 94306

For more information, contact Chimerix, Inc. at 1-866-662-2679.

This Instructions for Use has been approved by the U.S. Food and Drug Administration. Issued: 08/2025

PACKAGE/LABEL PRINCIPAL DISPLAY PANEL

RX ONLY

MODEYSO™
(dordaviprone)

125 mg
10 CAPSULES

FOR ORAL USE

See Full Prescribing Information
For MODEYSO Inside